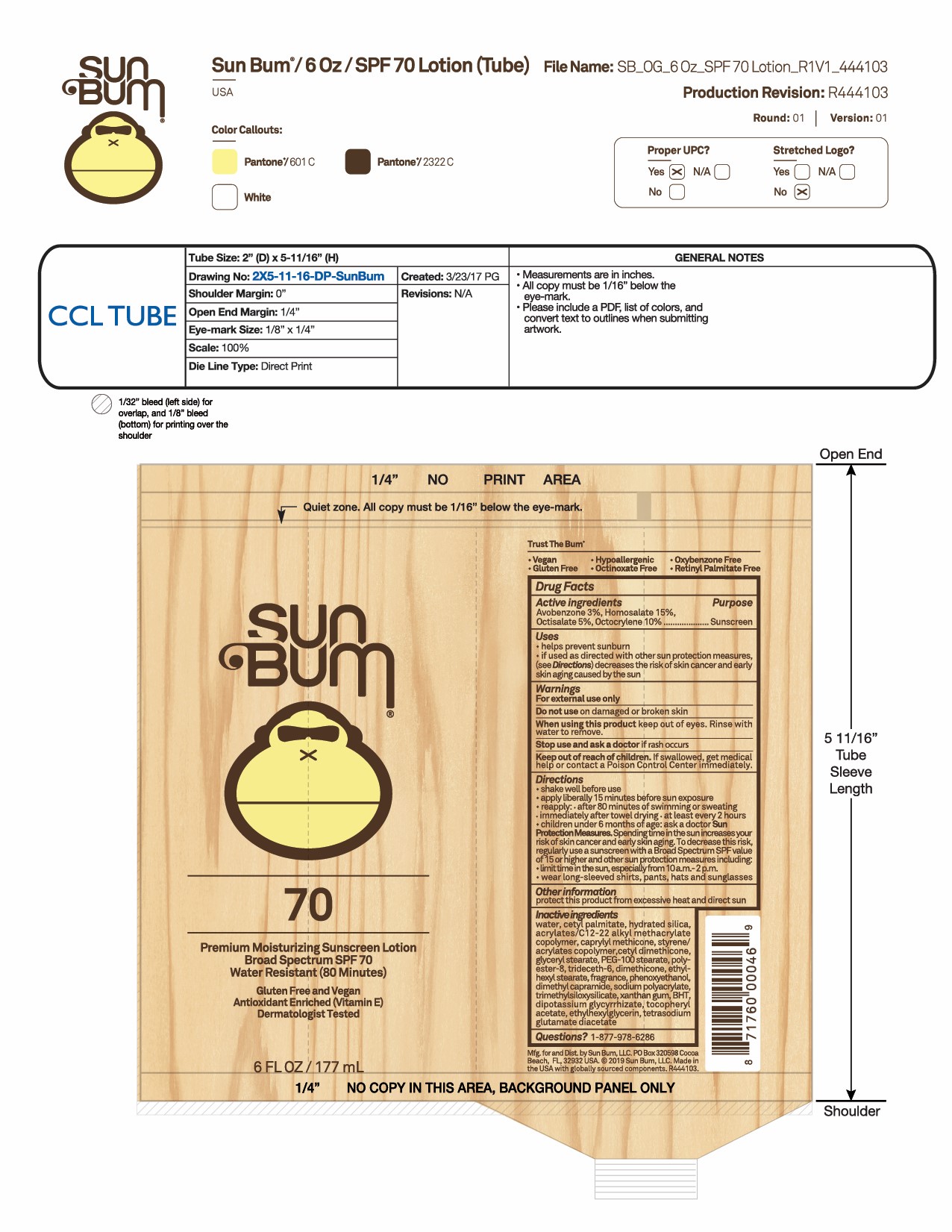 DRUG LABEL: Premium Moisturizing Sunscreen Broad Spectrum SPF 70
NDC: 44717-070 | Form: LOTION
Manufacturer: Wasatch Product Development, LLC
Category: otc | Type: HUMAN OTC DRUG LABEL
Date: 20251010

ACTIVE INGREDIENTS: AVOBENZONE 3 g/100 mL; HOMOSALATE 15 g/100 mL; OCTISALATE 5 g/100 mL; OCTOCRYLENE 10 g/100 mL
INACTIVE INGREDIENTS: ETHYLHEXYL STEARATE; CETYL DIMETHICONE 25; GLYCERYL MONOSTEARATE; PHENOXYETHANOL; DIMETHYL CAPRAMIDE; SODIUM POLYACRYLATE (8000 MW); TRIDECETH-6; DIMETHICONE 100; PEG-100 STEARATE; POLYESTER-8 (1400 MW, CYANODIPHENYLPROPENOYL CAPPED); TRIMETHYLSILOXYSILICATE (M/Q 0.6-0.8); GLYCYRRHIZINATE DIPOTASSIUM; WATER; HYDRATED SILICA; ETHYLHEXYLGLYCERIN; CAPRYLYL TRISILOXANE; CETYL PALMITATE; TETRASODIUM GLUTAMATE DIACETATE; .ALPHA.-TOCOPHEROL ACETATE; XANTHAN GUM; BUTYLATED HYDROXYTOLUENE

Sun Bum SPF 70 Premium Moisturizing Sunscreen Lotion

Active ingredients

Avobenzone 3%, Homosalate 15%, Octisalate 5%, Octocrylene 10%. Purpose: Sunscreen

Uses

- helps prevent sunburn
- if used as directed with other sun protection measures (see Directions), decreases the risk of skin cancer and early skin aging caused by the sun

Keep out of reach of children. If swallowed, get medical help or contact a Poison Control Center immediately.

Stop use and ask a doctor if rash occurs

Warnings

For external use only
Do not use on damaged or broken skin
When using this product keep out of eyes. Rinse with water to remove

Directions

- shake well before use
- apply liberally 15 minutes before sun exposure
- reapply:
- after 80 minutes of swimming or sweating
- immediately after towel drying
- at least every 2 hours.
- children under 6 months of age: ask a doctor.
- Sun Protection Measures Spending time in the sun increases your risk of

skin cancer and early skin aging. To decrease this risk, regularly use a
sunscreen with a Broad-Spectrum SPF value of 15 or higher and other sun
protection measures including:

• limit your time in the sun, especially from 10a.m. – 2 p.m.

• wear long-sleeved shirts, pants, hats, and sunglasses

Other information

Protect this product from excessive heat and direct sun

Inactive ingredients

water,cetyl palmitate, hydrated silica, acrylates/C12-22 alkyl methacrylate copolymer, caprylyl methicone, styrene/acrylates copolymer, cetyl dimethicone, glyceryl stearate, PEG-100 stearate, polyester-8, trideceth-6, dimethicone, ethylhexyl stearate, fragrance, phenoxyethanol, dimethyl capramide, sodium polyacrylate, trimethylsiloxysilicate, xanthan gum, BHT, dipotassium glycyrrhizate, tocopheryl acetate, ethylhexylglycerin, tetrasodium glutamate diacetate

PACKAGE LABEL

Sun Bum

70

Premium Moisturizing Sunscreen Lotion

Broad Spectrum SPF 70

Water Resistant (80 Minutes)

Gluten Free and Vegan

Antioxidant Enriched (Vitamin E)

Dermatologist Tested

6 FL OZ / 177 mL